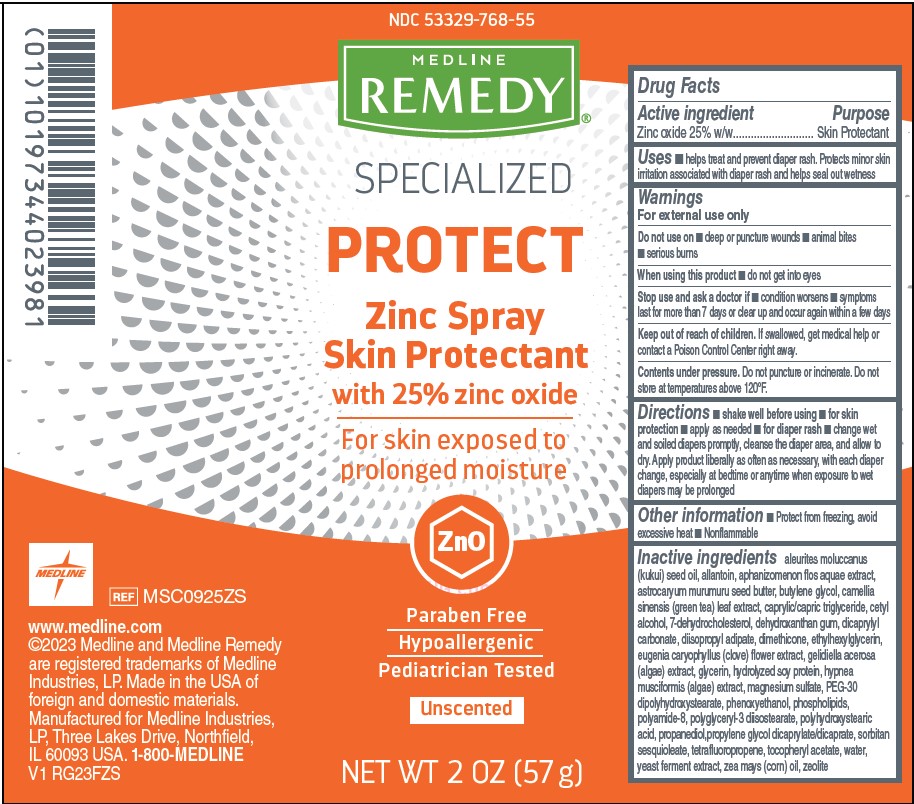 DRUG LABEL: Medline
NDC: 53329-768 | Form: SPRAY
Manufacturer: Medline Industries, LP
Category: otc | Type: HUMAN OTC DRUG LABEL
Date: 20251015

ACTIVE INGREDIENTS: ZINC OXIDE 250 mg/1 mL
INACTIVE INGREDIENTS: CAPRYLIC/CAPRIC TRIGLYCERIDE; .ALPHA.-TOCOPHEROL ACETATE; ALLANTOIN; APHANIZOMENON FLOSAQUAE; CETYL ALCOHOL; 1,3,3,3-TETRAFLUOROPROPENE, (1Z)-; CLOVE; OMEGA-3 FATTY ACIDS; PROPANEDIOL; PROPYLENE GLYCOL DICAPRYLATE/DICAPRATE; BUTYLENE GLYCOL; YEAST; GLYCERIN; MAGNESIUM SULFATE; DIMETHICONE; DICAPRYLYL CARBONATE; SORBITAN SESQUIOLEATE; ETHYLHEXYLGLYCERIN; HYDROLYZED SOY PROTEIN (ENZYMATIC; 2000 MW); HYPNEA MUSCIFORMIS; DIISOPROPYL ADIPATE; WATER; ZEA MAYS (CORN) OIL; POLYHYDROXYSTEARIC ACID (2300 MW); DEHYDROXANTHAN GUM; CAMELLIA SINENSIS LEAF; 7-DEHYDROCHOLESTEROL; ASTROCARYUM MURUMURU SEED BUTTER; PEG-30 DIPOLYHYDROXYSTEARATE; ZEOLITE A; KUKUI NUT OIL; GELIDIELLA ACEROSA; PHENOXYETHANOL; POLYAMIDE-8 (4500 MW); POLYGLYCERYL-3 DIISOSTEARATE

768 Zinc Barrier Spray

Active ingredient

Zinc oxide 25% w/w

Purpose

Skin Protectant

Uses

- helps treat and prevent diaper rash. Protects minor skin irritation associated with diaper rash and helps seal out wetness

Warnings

For external use only

Do not use on

- deep or puncture wounds
- animal bites
- serious burns

When using this product

- do not get into eyes

Stop use and ask a doctor

- condition worsens
- symptoms last for more than 7 days or clear up and occur again within a few days

Keep out of reach of children.

If swallowed, get medical help or contact a Poison Control Center right away.

Contents under pressure.

Do not puncture or incinerate. Do not store at temperatures above 120°F.

Directions

- shake well before using
- for skin protection
- apply as needed
- for diaper rash
- change wet and soiled diapers promptly, cleanse the diaper area, and allow to dry. Apply product liberally as often as necessary, with each diaper change, especially at bedtime or anytime when exposure to wet diapers may be prolonged

Other information

- Protect from freezing, avoid excessive heat
- Nonflammable

Inactive ingredients

aleurites moluccanus (kukui) seed oil, allantoin, aphanizomenon flos aquae extract, astrocaryum murumuru seed butter, butylene glycol, camellia sinensis (green tea) leaf extract, caprylic/capric triglyceride, cetyl alcohol, 7-dehydrocholesterol, dehydroxanthan gum, dicaprylyl carbonate, diisopropyl adipate, dimethicone, ethylhexylglycerin, eugenia caryophyllus (clove) flower extract, gelidiella acerosa (algae) extract, glycerin, hydrolyzed soy protein, hypnea musciformis (algae) extract, magnesium sulfate, PEG-30 dipolyhydroxystearate, phenoxyethanol, phospholipids, polyamide-8, polyglyceryl-3 diisostearate, polyhydroxystearic acid, propanediol, propylene glycol dicaprylate/dicaprate, sorbitan sesquioleate, tetrafluoropropene, tocopheryl acetate, water, yeast ferment extract, zea mays (corn) oil, zeolite

Manufacturing information

www.medline.com
©2023 Medline and Medline Remedy are registered trademarks of Medline Industries, LP.

Made in the USA of foreign and domestic materials.
Manufactured for Medline Industries, LP, Three Lakes Drive, Northfield, IL 60093 USA.

1-800-MEDLINE